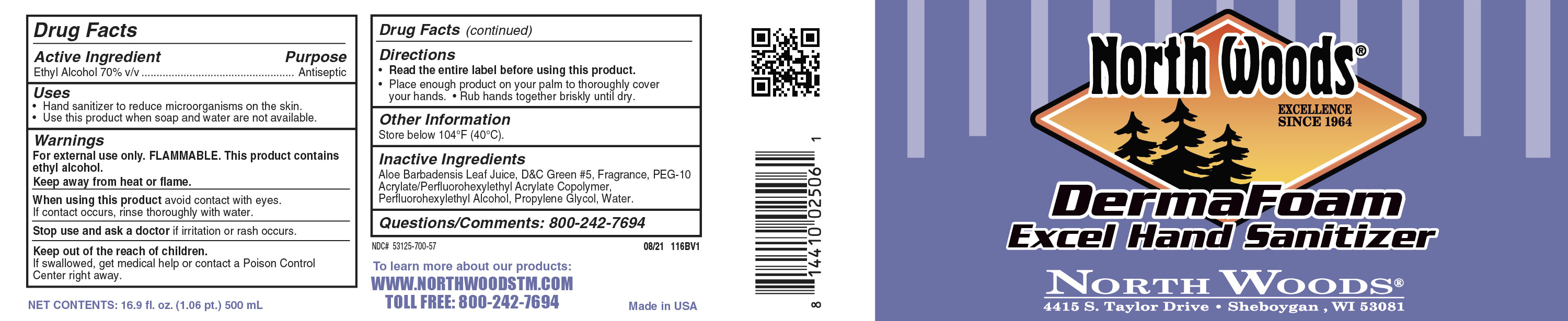 DRUG LABEL: ethanol
NDC: 53125-803 | Form: SOAP
Manufacturer: Superior Chemical Co DBA NorthWoods
Category: otc | Type: HUMAN OTC DRUG LABEL
Date: 20241227

ACTIVE INGREDIENTS: ALCOHOL 0.7 mL/1 mL
INACTIVE INGREDIENTS: HYDROXYCITRONELLAL; D&C GREEN NO. 5; 2-SEC-BUTYL CYCLOHEXANONE; WATER; 4-CYCLOHEXYL-2-METHYL-2-BUTANOL; ALOE VERA LEAF; HEXYL ACETATE; TETRAHYDROLINALOOL; ISOPROPYLPHENYLBUTANAL; 2-(PERFLUOROHEXYL)ETHANETHIOL; PEG-10 ACRYLATE/PERFLUOROHEXYLETHYL ACRYLATE COPOLYMER; PROPYLENE GLYCOL

Northwoods Derma Foam Excel Hand Sanitizer

Active ingredient

Ethyl Alcohol 70% V/V

Warning statement

Fore external use only. FLAMMABLE. This product contains ethyl alcohol. Keep away from heat or flame

purpose

Antiseptic

when using directions

when using this product avoid contact with eyes. if contact occurs, rinsth thoroughly wiht water.

Stop use and ask a doctor if irriataion or rash occurs

inactive ingredients

Aloe Barbadensis Leaf Juide, D&C Green #5, Fragrance, PER-10 Acrylate/perfluorohexylethly Acrylate copolymer, Perfluoroheexylethyl alcohol, propylene glycol, water

keep out of reach of children wording

Keep out of reach of children. If swallowed, get medical help or contact a Poison Control Center right away.

Directions for usage and dosage

Read entire label before using this product

Place enough product on your palm to thoroughly cover your hands. Rub hands together briskly until dry

indications and usage

Hand sanitizer to reduce microorganisms on the skin.

Use this product when soap and water are not available